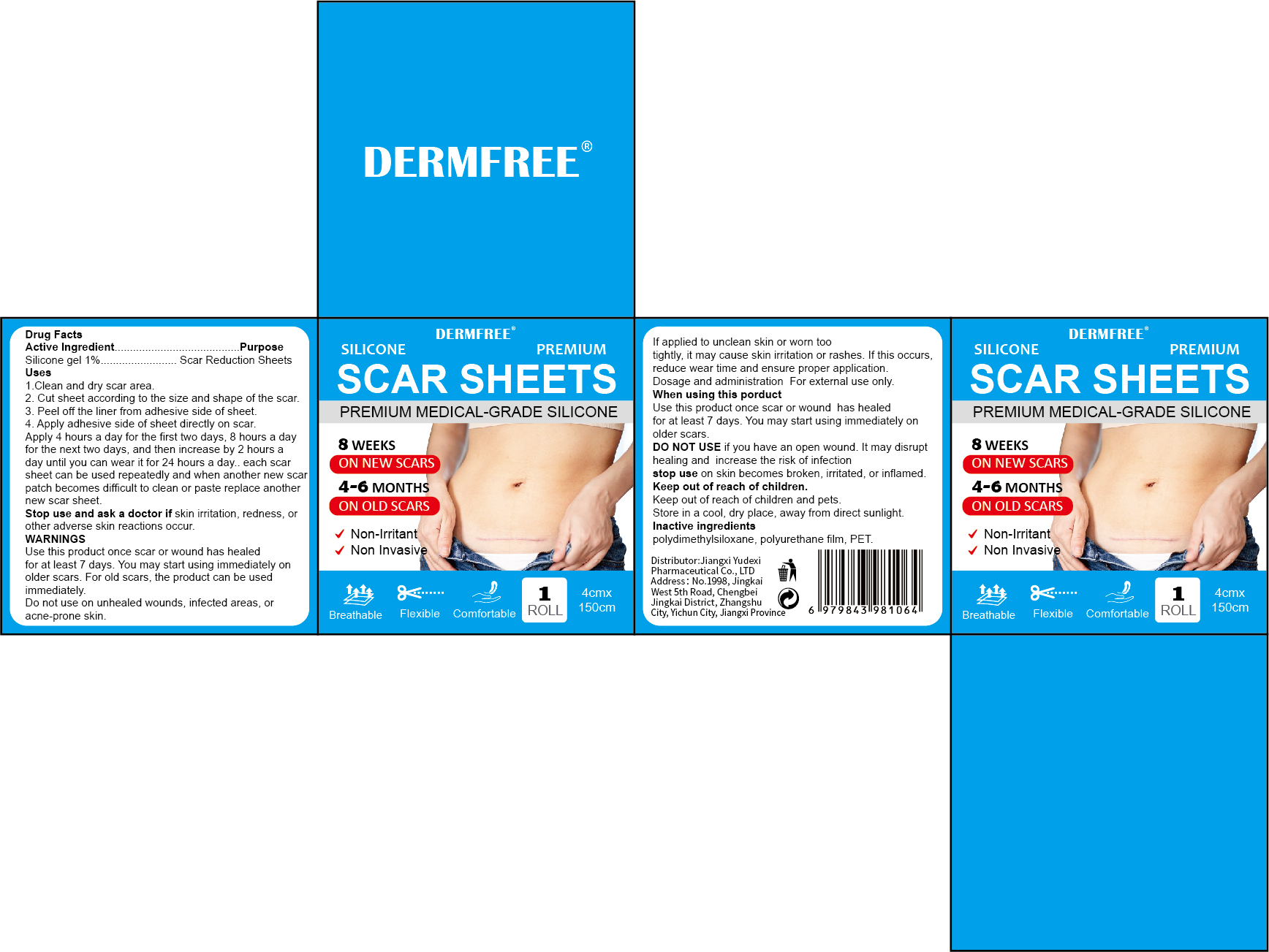 DRUG LABEL: DERMFREE SCAR SHEETS
NDC: 85248-110 | Form: PATCH
Manufacturer: Jiangxi Yudexi Pharmaceutical Co., LTD
Category: otc | Type: HUMAN OTC DRUG LABEL
Date: 20260208

ACTIVE INGREDIENTS: CYCLOMETHICONE 1 g/100 g
INACTIVE INGREDIENTS: POLYETHYLENE TEREPHTHALATE (INTRINSIC VISCOSITY 0.40-0.70); DIMETHICONE, UNSPECIFIED; POLYURETHANE-39

85248-110

Active Ingredient

Silicone gel 1%

Purpose

Scar Reduction Sheets

Use

1.Clean and dry scar area.
2.Cut sheet according to the size and shape of the scar.
3. Peel off the liner from adhesive side of sheet.
4. Apply adhesive side of sheet directly on scar.Apply 4 hours a day for the first two days, 8 hours a day for the next two days, and then increase by 2 hours aday until you can wear it for 24 hours a day. each scar sheet can be used repeatedly and when another new scar patch becomes difficult to clean or paste replace another new scar sheet.

Warnings

Use this product once scar or wound has healed for at least 7 days, You may start using immediately on older scars, For old scars, the product can be used immediately.
Do not use on unhealed wounds.infected areas. or acne-prone skin.
If applied to unclean skin or worn too tightly, it may cause skin irritation or rashes. If this occurs, reduce wear time and ensure proper application.
it should be reduced to stick and stick for less time. Dosage and administration For external use only.

Do not use on unhealed wounds, infected areas, or acne-prone skin.
If you have an open wound. It may disrupt healing and increase the risk of infection.

When Using

Use this product once scar or wound has healed for at least 7 days. You may start using immediately on older scars.

Stop Use

stop use on skin becomes broken, irritated, or inflamed

Ask Doctor

Stop use and ask a doctor if skin irritation, redness, or other adverse skin reactions occur.

Keep Oot Of Reach Of Children

Keep out of reach of children and pets.Store in a cool, dry place, away from direct sunlight.

Directions

Use this product once scar or wound has healed for at least 7 days, You may start using immediately on older scars, For old scars, the product can be used immediately.
Do not use on unhealed wounds.infected areas. or acne-prone skin.
If applied to unclean skin or worn too tightly, it may cause skin irritation or rashes. If this occurs, reduce wear time and ensure proper application.
it should be reduced to stick and stick for less time. Dosage and administration For external use only.

Inactive ingredients

polydimethylsiloxane, polyurethane film, PET.